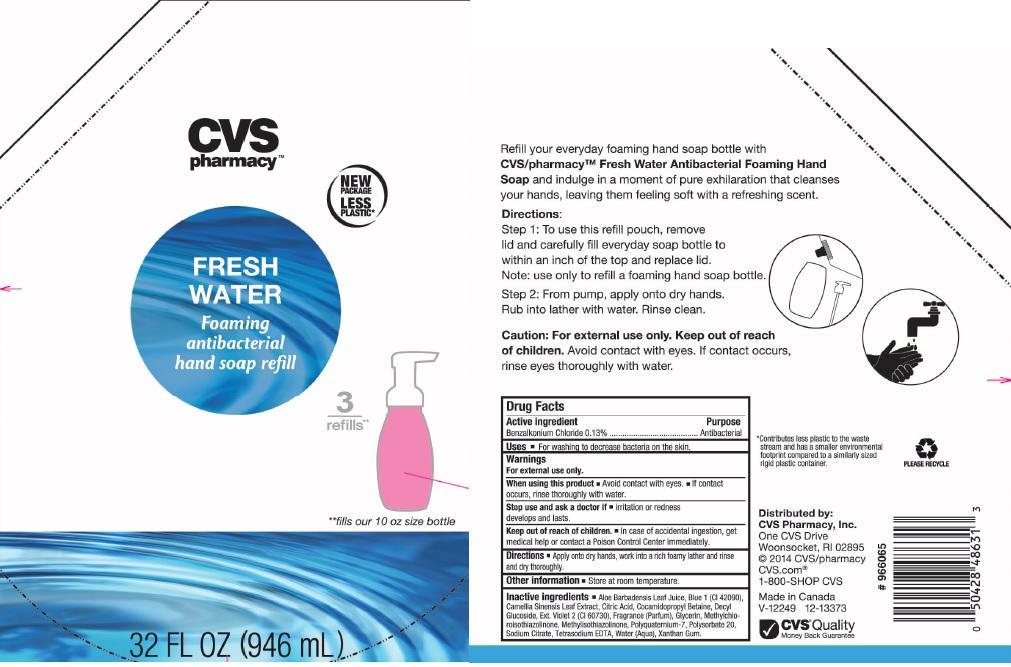 DRUG LABEL: CVS PHARMACY
NDC: 59779-114 | Form: LIQUID
Manufacturer: CVS PHARMACY
Category: otc | Type: HUMAN OTC DRUG LABEL
Date: 20140226

ACTIVE INGREDIENTS: BENZALKONIUM CHLORIDE 1.3 mg/1 mL
INACTIVE INGREDIENTS: ALOE VERA LEAF; FD&C BLUE NO. 1; GREEN TEA LEAF; CITRIC ACID MONOHYDRATE; COCAMIDOPROPYL BETAINE; DECYL GLUCOSIDE; EXT. D&C VIOLET NO. 2; GLYCERIN; METHYLCHLOROISOTHIAZOLINONE; METHYLISOTHIAZOLINONE; POLYQUATERNIUM-7 (70/30 ACRYLAMIDE/DADMAC; 1600000 MW); POLYSORBATE 20; SODIUM CITRATE; EDETATE SODIUM; WATER; XANTHAN GUM

DRUG FACTS

ACTIVE INGREDIENT

BENZALKONIUM CHLORIDE 0.13%

PURPOSE

ANTIBACTERIAL

USES

FOR WASHING TO DECREASE BACTERIA ON THE SKIN

WARNINGS

FOR EXTERNAL USE ONLY

WHEN USING THIS PRODUCT

AVOID CONTACT WITH EYES. IF CONTACT OCCURS, RINSE THOROUGH WITH WATER

STOP USE AND ASK A DOCTOR IF

IRRITATION OR REDNESS DEVELOPS AND LASTS

KEEP OUT OF REACH OF CHILDREN

IN CASE OF ACCIDENTAL INGESTION, GET MEDICAL HELP OR CONTACT A POISON CONTROL CENTER IMMEDIATELY

DIRECTIONS

APPLY ONTO DRY HANDS, WORK INTO A RICH FOAMY LATHER AND RINSE AND DRY THOROUGHLY

OTHER INFORMATION

STORE AT ROOM TEMPERATURE

INACTIVE INGREDIENTS

ALOE BARBADENSIS LEAF JUICE, BLUE 1 (CI 42090), CAMELLIA SINENSIS LEAF EXTRACT, CITRIC ACID, COCAMIDOPROPYL BETAINE, DECYL GLUCOSIDE, EXT. VIOLET 2 (CI 60730), FRAGRANCE (PARFUM), GLYCERIN, METHYLCHLOROISOTHIAZOLINONE, METHYLISOTHIAZOLINONE, POLYQUATERNIUM-7, POLYSORBATE 20, SODIUM CITRATE, TETRASODIUM EDTA, WATER (AQUA), XANTHAN GUM